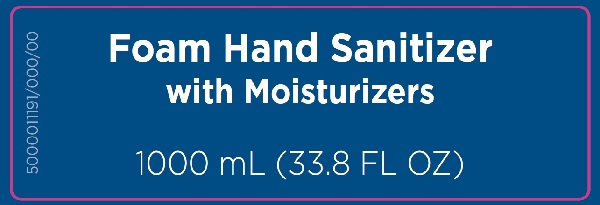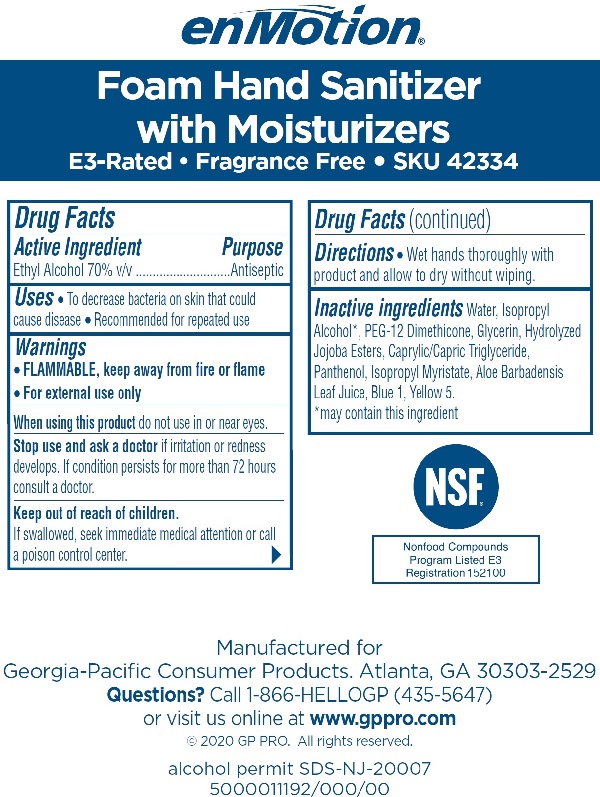 DRUG LABEL: enMotion Foam Sanitizer with Moisturizers Fragrance Free
NDC: 54622-423 | Form: SOLUTION
Manufacturer: Georgia Pacific Consumer Products
Category: otc | Type: HUMAN OTC DRUG LABEL
Date: 20210323

ACTIVE INGREDIENTS: ALCOHOL 70 mg/1 mL
INACTIVE INGREDIENTS: WATER; ISOPROPYL ALCOHOL; PEG-12 DIMETHICONE; GLYCERIN; HYDROLYZED JOJOBA ESTERS (ACID FORM); MEDIUM-CHAIN TRIGLYCERIDES; PANTHENOL; ISOPROPYL MYRISTATE; ALOE VERA LEAF; FD&C BLUE NO. 1; FD&C YELLOW NO. 5

enMotion Foam Sanitizer with Moisturizers, Fragrance Free

Active Ingredient

Ethyl Alcohol 70% v/v

Purpose

Antiseptic

Uses

- To decrease bacteria on skin that could cause disease
- Recommended for repeated use

Warnings

- FLAMMABLE, keep away from fire or flame
- For external use only

When using this product do not use in or near eyes.

Stop use and ask a doctor if irritation or redness develops. If condition persists for more than 72 hours consult a doctor.

Keep out of reach of children.

If swallowed, seek immediate medical attention or call a poison control center.

Directions

- Wet hands thoroughly with product and allow to dry without wiping.

Inactive ingredients

Water, Isopropyl Alcohol*, PEG-12 Dimethicone, Glycerin, Hydrolyzed Jojoba Esters, Caprylic/Capric Triglyceride, Panthenol, Isopropyl Myristate, Aloe Barbadensis Leaf Juice, Blue 1, Yellow 5.

*may contain this ingredient

Rear Label Text

enMotion®

Foam Hand Sanitizer with Moisturizers

E3-Rated • Fragrance Free • SKU 42334

Manufactured for

Georgia-Pacific Consumer Products. Atlanta, GA 30303-2529

Questions? Call 1-866-HELLOGP (435-5647)

or visit us online at www.gppro.com

©2020 GP PRO. All rights reserved.

alcohol permit SDS-NJ-20007

5000011192/000/00

PACKAGE LABEL

Foam Hand Sanitizer with Moisturizers

1000 mL (33.8 FL OZ)

NDC - 54622-423-01